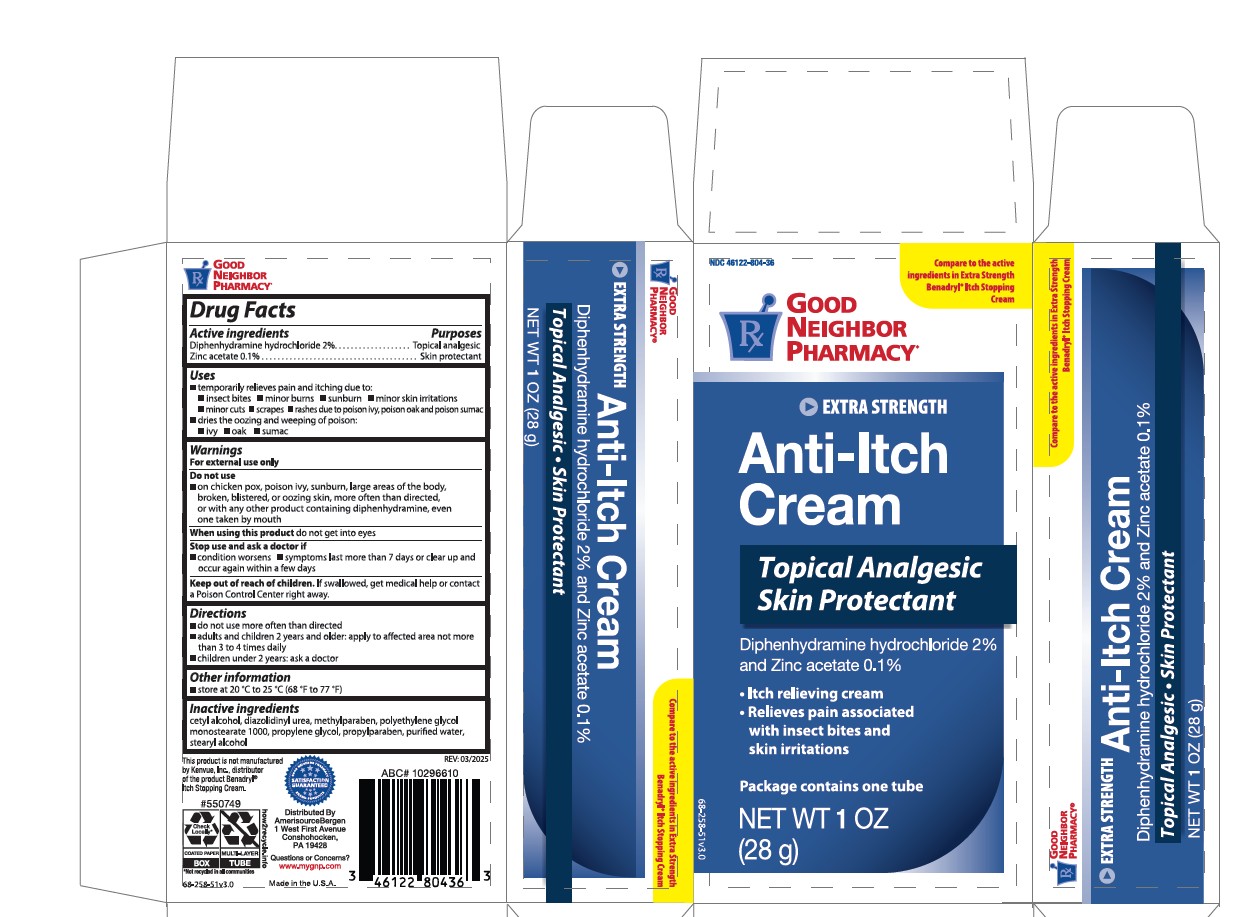 DRUG LABEL: GNP Extra Strength Anti-Itch Cream
NDC: 46122-804 | Form: CREAM
Manufacturer: Amerisource Bergen
Category: otc | Type: HUMAN OTC DRUG LABEL
Date: 20250508

ACTIVE INGREDIENTS: ZINC ACETATE 0.1 g/100 g; DIPHENHYDRAMINE HCL 2 g/100 g
INACTIVE INGREDIENTS: POLYETHYLENE GLYCOL 1000; DIAZOLIDINYL UREA; METHYLPARABEN; PROPYLENE GLYCOL; CETYL ALCOHOL; STEARYL ALCOHOL; WATER; PROPYLPARABEN

Active Ingredients

Diphenhydramine hydrochloride 2%

Zinc acetate 0.1%

Ask Doctor Section

conditions worsen

symptoms last more than 7 days or clear up and occur again within a few days

Do not use section

on chicken pox, poison ivy, sunburn, large areas of the body, broken, blistered, or oozing skin, more often than directed, or with any other product containing diphenhydramine, even one taken by mouth

KEEP OUT OF REACH OF CHILDREN

If swallowed, get medical help or contact a Poison Control Center right away.

WARNINGS

For external use only

Directions

do not use more often then directed

adults and children 2 years and older: apply to affected area not more than 3 to 4 times daily

children under 2 years: ask doctor

Uses

temporarily relieves pain and itching due to:

- insect bites
- minor burns
- sunburns
- minor skin irritations
- minor cuts
- scrapes
- rashes due to poison ivy, poison oak and poison sumac
- dries the oozing and weeping of poison:
  - Ivy
  - oak
  - sumac

OTHER SAFETY INFORMATION

Store at 20C to 25C (68F to 77F)

QUESTIONS

www.mygnp.com

INACTIVE INGREDIENT

ceytl alcohol

diazolindinyl urea

methlparaben

polyethylene glycol

monostearate 1000

propylene glycol

propylparaben

purified water

stearyl alcohol

PURPOSE

Diphenhydramine hydrochloride...............Topical anagesic

Zinc acetate..............................................Skin protectant